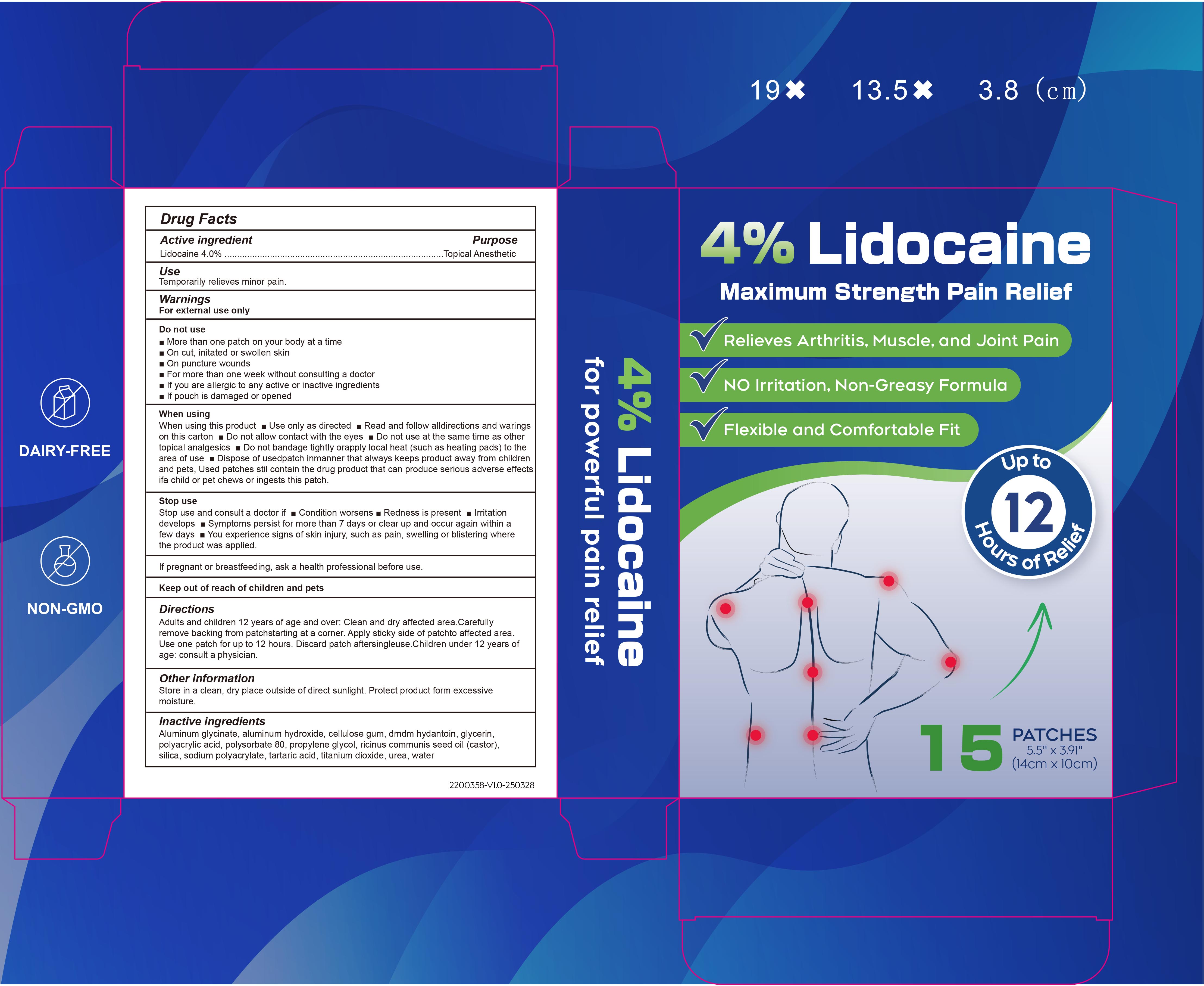 DRUG LABEL: 4% Lidocaine Maximum Strength Pain Relief
NDC: 85839-011 | Form: PATCH
Manufacturer: Shenzhen Finona Information Technology Co., Ltd
Category: otc | Type: HUMAN OTC DRUG LABEL
Date: 20251203

ACTIVE INGREDIENTS: LIDOCAINE 0.04 g/1 1
INACTIVE INGREDIENTS: PROPYLENE GLYCOL; ALUMINUM HYDROXIDE; POLYSORBATE 80; SODIUM POLYACRYLATE (2500000 MW); DMDM HYDANTOIN; TARTARIC ACID; SILICA; GLYCERIN; RICINUS COMMUNIS (CASTOR) SEED OIL; TITANIUM DIOXIDE; UREA; CELLULOSE GUM; ALUMINUM GLYCINATE; WATER; POLYACRYLIC ACID (250000 MW)

85839-011 4% Lidocaine Maximum Strength Pain Relief

ACTIVE INGREDIENT

Lidocaine 4%

PURPOSE

Topical Anesthetic

INDICATIONS AND USAGE

Use Temporarily relieves minor paln.

WARNINGS

For external use only

Do not use More than one patch on your body at a time On cut, initated orswollen skin On puncture wounds For more than one week without consultinga doctor lf you are allergic to any active or inactive ingredients lf pouch isdamaged or opened.

When using this product Use only as directed Read and follow alldirections and warings on this carton Do not allow contact with the eyes Do not use at the same time as other topical analgesics Do not bandage tightly orapply local heat (such as heating pads) to the area of use Dispose of usedpatch inmanner that always keeps product away from children and pets. Usedpatches stil contain the drug product that can produce serious adverse effects ifa child or pet chews or ingests this patch.

Stop use and consult a doctor if Condition worsens Redness is presentlrritation develops Symptoms persist for more than 7 days or clear up and occur again within a few days You experience signs of skin injury, such as pain, swelling or blistering where the product was applied.

Keep out of reach of children and pets.

DOSAGE AND ADMINISTRATION

Adults and children 12 years of age and over:
Clean and dry affected area Carefully remove backing from patchstarting at a corner. Apply sticky side of patch to affected area. Use one patch for up to 12 hours. Discard patch aftersingle use.Children under 12 years of age: consult a physician.

INACTIVE INGREDIENT

Aluminum Glycinate
Aluminum Hydroxide
Cellulose Gum
DMDM hydantoin
Glycerin
Polyacrylic Acid
Polysorbate 80
Propylene Glycol
Ricinus Communis Seed Oil (castor)
Silica
Sodium Polyacrylate
Tartaric Acid
Titanium Dioxide
Urea
Water